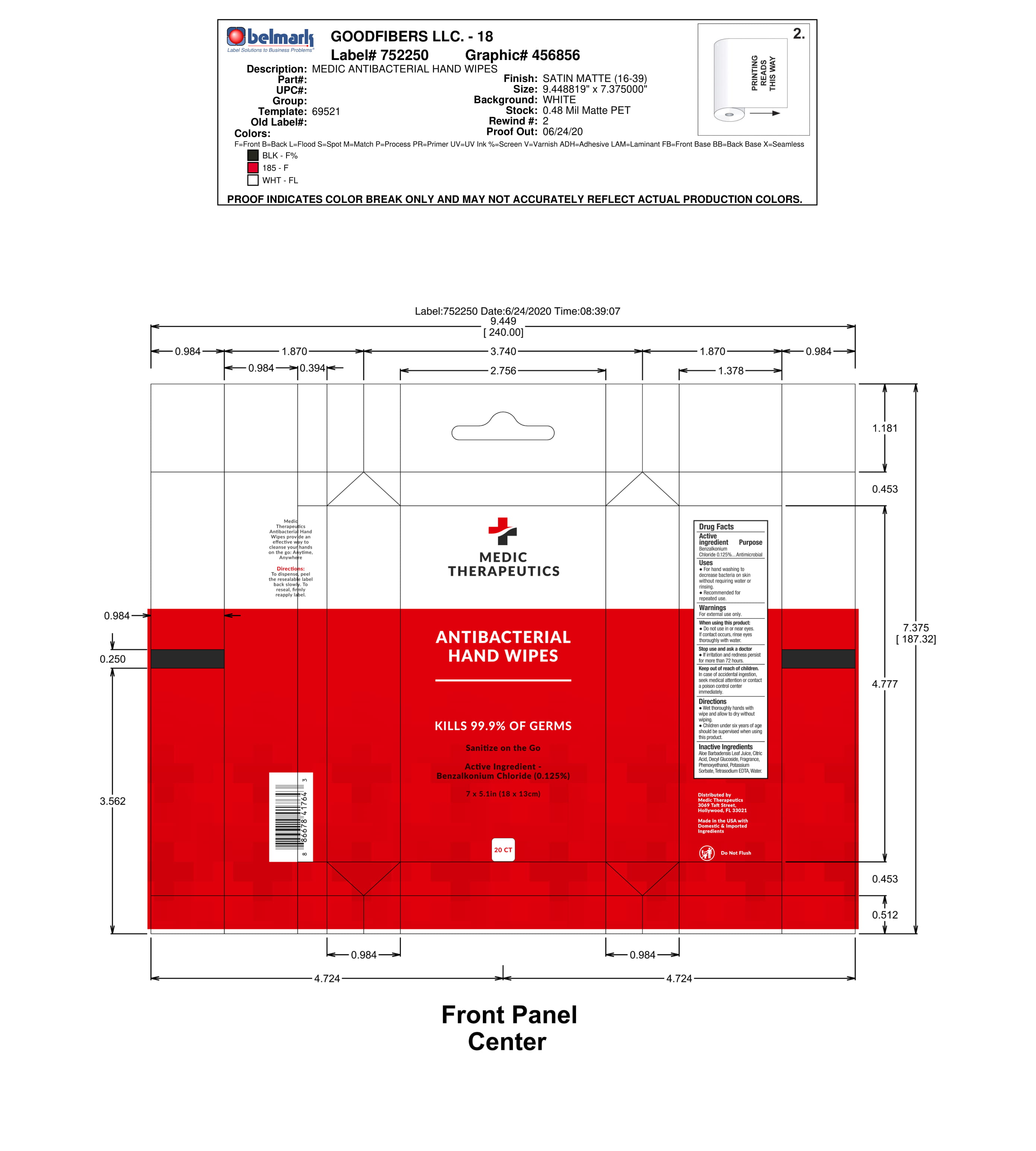 DRUG LABEL: Antibacterial Hand Wipes
NDC: 77070-702 | Form: CLOTH
Manufacturer: GoodFibers
Category: otc | Type: HUMAN OTC DRUG LABEL
Date: 20220122

ACTIVE INGREDIENTS: BENZALKONIUM CHLORIDE 0.125 g/100 g
INACTIVE INGREDIENTS: ALOE VERA LEAF; PHENOXYETHANOL; WATER; ANHYDROUS CITRIC ACID; DECYL GLUCOSIDE; EDETATE SODIUM; POTASSIUM SORBATE

Antibacterial Hand Wipes

Active Ingredient

Benzalkonium

Chloride 0.125%

Purpose

Antimicrobial

USES

*For hand washing to decrease bacteria on skin without requiring water or rinsing.

*Recommended for repeated use

Warnings

For external use only.

When using product

*Do not use in or near eyes.

If contact occurs, rinse eyes thoroughly with water.

Stop use and ask a doctor

*If irritation and redness persist for more than 72 hours.

Keep out of reach of children

In case of accidental indestion, seek medical attention or contact a poison control center immediately.

Directions

*Wet thoroughly hands with wipe and allow to dry without wiping.

*Children under six years of age should be supervised when using this product.

Inactive Ingredients

Aloe Barbadensis Leaf Juice, Citric Acid, Decyl Glucoside, Fragrtance, Phenoxyethanol, Potassium Sorbate, Tetrasodium EDTA, Water.

PDP

MEDIC THERAPEUTICS

ANTIBACTERIAL

HAND WIPES

___________________

KILLS 99.9% OF GERMS

Sanitize on the Go

Active Ingredient -

Benzalkonium Chloride (0.125%)

7 x 5.1in (18 x 13 cm)

20 CT